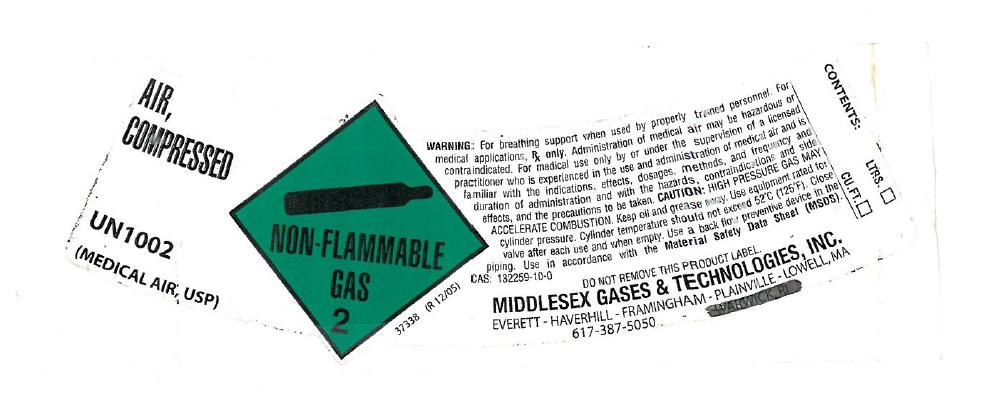 DRUG LABEL: Air
NDC: 63961-003 | Form: GAS
Manufacturer: Middlesex Gases and Technologies, Inc.
Category: prescription | Type: HUMAN PRESCRIPTION DRUG LABEL
Date: 20111101

ACTIVE INGREDIENTS: Air 1000 mL/1 L

air

PACKAGE LABEL

AIR, COMPRESSED UN 1002 MEDICAL AIR, USP
NON-FLAMMABLE GAS 2
WARNING: For breathing support when used by properly trained personnel. For medical applications, Rx only. Administration of medical air may be hazardous or contraindicated. For medical use only be or under the supervision of a licensed practitioner who is experienced in the use and administration of medical air and is familiar with the indications, effects, dosages, methods, and frequency and duration of administration and with the hazards of contraindications and side effects, and the precautions to be taken.
CAUTION! HIGH PRESSURE GAS. MAY ACCELERATE COMBUTION.
Keep oil, grease and combustibles away. Keep away from heat, flame and sparks. Use equipment rated for cylinder pressure. Cylinder temperate should not exceed 52 degrees C (125 degrees F). Close valve when not in use and when empty. Use a back flow preventive device in the piping. Use in accordance with Material Safety Data Sheet (MSDS).
CAS 132259-10-0
DO NOT REMOVE THIS PRODUCT LABEL.
MIDDLESEX GASES AND TECHNOLOGIES, INC.
EVERETT. HAVERHILL. FRAMINGHAM. PLAINVILLE. LOWELL, MA
617-387-5050